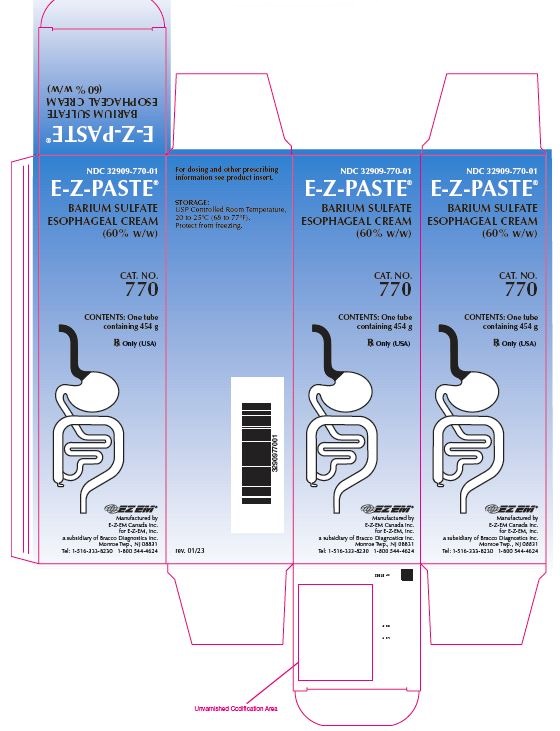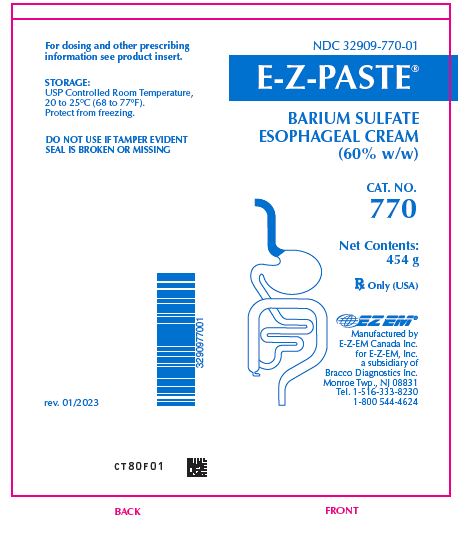 DRUG LABEL: E-Z-Paste
NDC: 32909-770 | Form: CREAM
Manufacturer: E-Z-EM Canada Inc
Category: prescription | Type: HUMAN PRESCRIPTION DRUG LABEL
Date: 20251218

ACTIVE INGREDIENTS: BARIUM SULFATE .6 g/1 g
INACTIVE INGREDIENTS: CARBOXYMETHYLCELLULOSE SODIUM; DIMETHICONE 350; DIMETHICONE 1000; ETHYL VANILLIN; GLYCERIN; METHYLPARABEN; PROPYLPARABEN; SACCHARIN SODIUM; SILICON DIOXIDE; SORBITOL; TRISODIUM CITRATE DIHYDRATE; WATER; ANHYDROUS CITRIC ACID

NDC 32909-770-01
E-Z-PASTE®
BARIUM SULFATE ESOPHAGEAL CREAM
(60% w/w)

DESCRIPTION

E-Z-PASTE® Barium Sulfate Esophageal Cream (60% w/w) is a barium sulfate cream for oral administration. Each 100 g contains 60 g barium sulfate. Barium sulfate, due to its high molecular density is opaque to x-rays and, therefore, acts as a positive contrast agent for radiographic studies. The active ingredient is barium sulfate and its structural formula is BaSO4. Barium sulfate occurs as a fine, white, odorless, tasteless, bulky powder which is free from grittiness. Its aqueous suspensions are neutral to litmus. It is practically insoluble in water, solutions of acids and alkalies, and organic solvents.

INACTIVE INGREDIENT

Inactive Ingredients: carboxymethylcellulose sodium, citric acid, ethyl vanillin, glycerin, methylparaben, propylparaben, purified water, saccharin sodium, simethicone emulsion, sodium citrate, and sorbitol solution.

CLINICAL PHARMACOLOGY

Barium sulfate, due to its high molecular density is opaque to x-rays and, therefore, acts as a positive contrast agent for radiographic studies. Barium sulfate is biologically inert and therefore, is not absorbed or metabolized by the body, and is eliminated unchanged from the body.

INDICATIONS AND USAGE

For use in single contrast radiography of the esophagus, pharynx, hypopharynx and for cardiac series.

CONTRAINDICATIONS

This product should not be used in patients with known gastric or intestinal perforation or hypersensitivity to barium sulfate products.

WARNINGS

Rarely, severe allergic reactions of an anaphylactoid nature, have been reported following administration of barium sulfate contrast agents. Appropriately trained personnel and facilities should be available for emergency treatment of severe reactions and should remain available for at least 30 to 60 minutes following administration, since delayed reactions can occur.

PRECAUTIONS

General

Diagnostic procedures which involve the use of radiopaque contrast agents should be carried out under the direction of personnel with the requisite training and with a thorough knowledge of the particular procedure to be performed. A history of bronchial asthma, atopy, as evidenced by hay fever and eczema, or a previous reaction to a contrast agent, warrant special attention. Caution should be exercised with the use of radiopaque media in severely debilitated patients and in those with marked hypertension or advanced cardiac disease.

Caution should be used during the administration of this product to patients with a history of food aspiration or to patients in whom integrity of the swallowing mechanism is unknown. If this product is aspirated into the larynx, further administration should be discontinued immediately.

After any barium study of the GI tract, it is important to rehydrate the patient as quickly as possible to prevent impaction of the bowel by barium sulfate. To prevent barium sulfate impaction in the bowel, the use of mild laxatives such as milk of magnesia or lactulose, following completion of the examination may also be required. These mild laxatives are recommended on a routine basis and in patients with a history of constipation unless contraindicated.

Use with caution with complete or nearly complete esophageal or gastric obstruction.

Information for Patients

Before administration of this product patients should be instructed to:

1. Inform their physician if they are pregnant.
2. Inform their physician if they are allergic to any drugs or food, or if they have had any prior reactions to barium sulfate products or other contrast agents used in x-ray procedures (see PRECAUTIONS-General).
3. Inform their physician about any other medications they are currently taking.

Drug Interactions

The presence of barium sulfate formulations in the GI tract may alter the absorption of therapeutic agents taken concomitantly. In order to minimize any potential change in absorption, the separate administration of barium sulfate from that of other agents should be considered.

Usage in Pregnancy

Radiation is known to cause harm to the unborn fetus exposed in utero. Therefore, radiographic procedures should only be used when, in the judgement of the physician, its use is deemed essential to the welfare of the pregnant patient.

Nursing Mothers

Barium sulfate products may be used during lactation.

ADVERSE REACTIONS

Adverse reactions, such as nausea, vomiting, diarrhea and abdominal cramping, accompanying the use of barium sulfate formulations are infrequent and usually mild. Severe reactions (approximately 1 in 1,000,000) and fatalities (approximately 1 in 10,000,000) have occurred. Procedural complications are rare, but may include aspiration pneumonitis, barium sulfate impaction, granuloma formation, intravasation, embolization and peritonitis following intestinal perforation, vasovagal and syncopal episodes, and fatalities. It is of the utmost importance to be completely prepared to treat any such occurrence.

ALLERGIC REACTIONS

Due to the increased likelihood of allergic reactions in atopic patients, it is important that a complete history of known and suspected allergies as well as allergic-like symptoms, e.g., rhinitis, bron-chial asthma, eczema and urticaria, must be obtained prior to any medical procedure utilizing these products. A mild allergic reaction would most likely include generalized pruritus, erythema or urticaria (approximately 1 in 250,000). Such reactions will generally respond to an antihistamine such as 50 mg of diphenhydramine or its equivalent. In the rarer, more serious reactions (approximately 1 in 1,000,000) laryngeal edema, bronchospasm or hypotension could develop. Severe reactions which may require emergency measures are often characterized by peripheral vasodilation, hypotension, reflex tachycardia, dyspnea, agitation, confusion and cyanosis progressing to unconsciousness. Treatment should be initiated immediately with 0.3 to 0.5 mL of 1:1000 epinephrine subcutaneously. If bronchospasm predominates, 0.25 to 0.50 grams of intravenous aminophylline should be given slowly. Appropriate vasopressors might be required. Adrenocorticosteroids, even if given intravenously, exert no significant effect on the acute allergic reactions for a few hours. The administration of these agents should not be regarded as emergency measures for the treatment of allergic reactions.

Apprehensive patients may develop weakness, pallor, tinnitus, diaphoresis and bradycardia following the administration of any diagnostic agent. Such reactions are usually non-allergic in nature and are best treated by having the patient lie flat for an additional 10 to 30 minutes under observation.

OVERDOSAGE

On rare occasions following repeated administration, severe stomach cramps, nausea, vomiting, diarrhea or constipation may occur. These are transitory in nature and are not considered serious. Symptoms may be treated according to currently accepted standards of medical care.

DOSAGE AND ADMINISTRATION

Usual dose is one to four teaspoons as required.

Storage

Store product at USP Controlled Room Temperature, 20 to 25°C (68 to 77°F). Protect from freezing.

HOW SUPPLIED

E-Z-PASTE® is supplied in the following quantity:
454 g Tube, Cat. No. 770; NDC 32909-770-01

Manufactured by E-Z-EM Canada Inc.
for E-Z-EM, Inc.
a subsidiary of Bracco Diagnostics Inc.
Monroe Township, NJ 08831
Tel: 1-516-333-8230 1-800 544-4624

rev. 10/17 CL80E01 TX1887

PACKAGE LABEL

E-Z-Paste - Barium Sulfate Esophageal Cream

NDC: 32909-770-01

CL80E02

rev. 01/2023

PACKAGE LABEL

E-Z-Paste - Carton